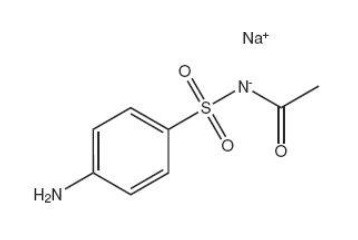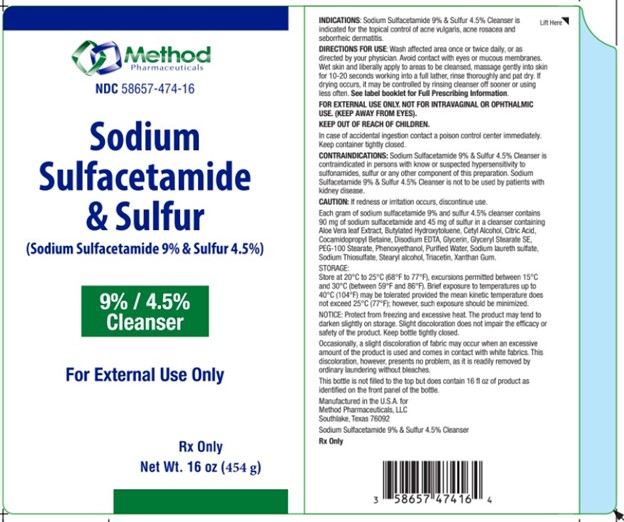 DRUG LABEL: Sodium Sulfacetamide 9% and Sulfur 4% Cleanser
NDC: 58657-473 | Form: LIQUID
Manufacturer: Method Pharmaceuticals
Category: prescription | Type: HUMAN PRESCRIPTION DRUG LABEL
Date: 20260212

ACTIVE INGREDIENTS: SULFACETAMIDE SODIUM 90 mg/1 mL; SULFUR 40 mg/1 mL
INACTIVE INGREDIENTS: PHENOXYETHANOL; TRIACETIN; ALOE VERA LEAF; BUTYLATED HYDROXYTOLUENE; COCAMIDOPROPYL BETAINE; CETYL ALCOHOL; EDETATE DISODIUM; GLYCERYL STEARATE SE; PEG-100 STEARATE; WATER; SODIUM THIOSULFATE; SODIUM LAURYL SULFATE; STEARYL ALCOHOL; XANTHAN GUM

Sodium Sulfacetamide 9% - Sulfur 4% Cleanser

Rx Only

DESCRIPTION

Each gram of sodium sulfacetamide 9% and sulfur 4% cleanser contains 90 mg of sodium sulfacetamide and 40 mg of sulfur in a cleanser containing Aloe Vera leaf Extract, Butylated Hydroxytoluene, Cetyl Alcohol, Citric Acid, Cocamidopropyl Betaine, Disodium EDTA, Glycerin, Glyceryl Stearate SE, PEG-100 Stearate, Phenoxyethanol, Purified Water, Sodium laureth sulfate, Sodium Thiosulfate, Stearyl alcohol, Triacetin, Xanthan Gum.
Sodium sulfacetamide is a sulfonamide with antibacterial activity while sulfur acts as a keratolytic agent. Sodium sulfacetamide is C8H9N2NaO 3S·H2O with molecular weight of 254.24. Chemically, it is N-[(4-aminophenyl)sulfonyl]-acetamide, monosodium salt, monohydrate.

The structural formula is:

Clinical Pharmacology

Sodium sulfacetamide exerts a bacteriostatic effect against sulfonamide sensitive Gram-positive and Gram-negative microorganisms commonly isolated from secondary cutaneous pyogenic infections. It acts by restricting the synthesis of folic acid required by bacteria for growth, by its competition with para-aminobenzoic acid. There is no clinical data available on the degree and rate of systemic absorption of this product when applied to the skin or scalp. However, significant absorption of sodium sulfacetamide through the skin has been reported.

The following in vitro data is available but the clinical significance is unknown. Organisms that show susceptibility to sodium sulfacetamide are: Streptococci, Staphylococci, E. coli, Klebsiella pneumoniae, Pseudomonas pyocyanea, Salmonella species, Proteus vulgaris, Nocardia and Actinomyces.

The exact mode of action of sulfur in the treatment of acne is unknown, but it has been reported that it inhibits the growth of Propionibacterium acnes and the formation of free fatty acids.

INDICATIONS

SODIUM SULFACETAMIDE 9% - SULFUR 4% CLEANSER is indicated for use in the topical control of acne vulgaris, acne rosacea and seborrheic dermatitis.

CONTRAINDICATIONS:

SODIUM SULFACETAMIDE 9% - SULFUR 4% CLEANSER is contraindicated for use by patients having known hypersensitivity to sulfonamides, sulfur or any other component of this preparation. SODIUM SULFACETAMIDE 9% - SULFUR 4% CLEANSER is not to be used by patients with kidney disease.

WARNINGS

Although it is rare, sensitivity to sodium sulfacetamide may occur. Therefore, caution and careful supervision should be observed when prescribing this drug for patients who may be prone to hypersensitivity to topical sulfonamides. Systemic toxic reactions such as agranulocytosis, acute hemolytic anemia, purpura hemorrhagica, drug fever, jaundice, and contact dermatitis indicate hypersensitivity to sulfonamides. Particular caution should be employed if areas of denuded or abraded skin are involved.

FOR EXTERNAL USE ONLY. NOT FOR INTRAVAGINAL OR OPHTHALMIC USE. (KEEP AWAY FROM EYES).

KEEP OUT OF REACH OF CHILDREN.

In case of accidental ingestion contact a poison control center immediately. Keepcontainer tightly closed.

Precaution

General: If irritation develops, use of the product should be discontinued and appropriate therapy instituted. Patients should be carefully observed for possible local irritation or sensitization during long-term therapy. The object of this therapy is to achieve desquamation without irritation, but sodium sulfacetamide and sulfur can cause reddening and scaling of the epidermis. These side effects are not unusual in the treatment of acne vulgaris, but patients should be cautioned about the possibility.

Information for Patients: Avoid contact with eyes, eyelids, lips and mucous membranes. If accidental contact occurs, rinse with water. If excessive irritation develops, discontinue use and consult your physician.

Carcinogenesis, Mutagenesis and Impairment of Fertility: Long-term studies in animals have not been performed to evaluate carcinogenic potential.

Pregnancy: Category C. Animal reproduction studies have not been conducted with Sodium Sulfacetamide 9% & Sulfur 4% Cleanser. It is also not known whether Sodium Sulfacetamide 9% & Sulfur 4% Cleanser can cause fetal harm when administered to a pregnant woman or can affect reproduction capacity. Sodium Sulfacetamide 9% & Sulfur 4% Cleanser should be given to a pregnant woman only if clearly needed.

Nursing Mothers: It is not known whether sodium sulfacetamide is excreted in the human milk following topical use of Sodium Sulfacetamide 9% & Sulfur 4% Cleanser. However, small amounts of orally administered sulfonamides have milk. In view of this and because many drugs are excreted in human milk, caution should be exercised when Sodium Sulfacetamide 9% & Sulfur 4% Cleanser is administered to a nursing woman.

Pediatric Use: Safety and effectiveness in children under the age of 12 have not been established.

Adverse Reaction

Although rare, sodium sulfacetamide may cause local irritation.

Call your doctor for medical advice about side effects.

To report a serious adverse event or obtain product information, call 1-877-250-3427.

DOSAGE AND ADMINISTRATION

Wash affected area once or twice daily, or as directed by your physician. Avoid contact with eyes or mucous membranes. Wet skin and liberally apply to areas to be cleansed, massage gently into skin for 10-20 seconds working into a full lather, rinse thoroughly and pat dry. If drying occurs, it may be controlled by rinsing cleanser off sooner or using less often.

See label booklet for Full Prescribing Information.

HOW SUPPLIED

Store at 20°C to 25°C (68°F to 77°F), excursions permitted between 15°C and 30°C (between 59°F and 86°F). Brief exposure to temperatures up to 40°C (104°F) may be tolerated provided the mean kinetic temperature does not exceed 25°C (77°F); however, such exposure should be minimized.

NOTICE: Protect from freezing and excessive heat. The product may tend to darken slightly on storage. Slight discoloration does not impair the efficacy or safety of the product. Keep bottle tightly closed. Occasionally, a slight discoloration of fabric may occur when an excessive amount of the product is used and comes in contact with white fabrics. This discoloration, however, presents no problem, as it is readily removed by ordinary laundering without bleaches.

This bottle is not filled to the top but does contain 16 fl oz of product as identified on the front panel of the bottle.